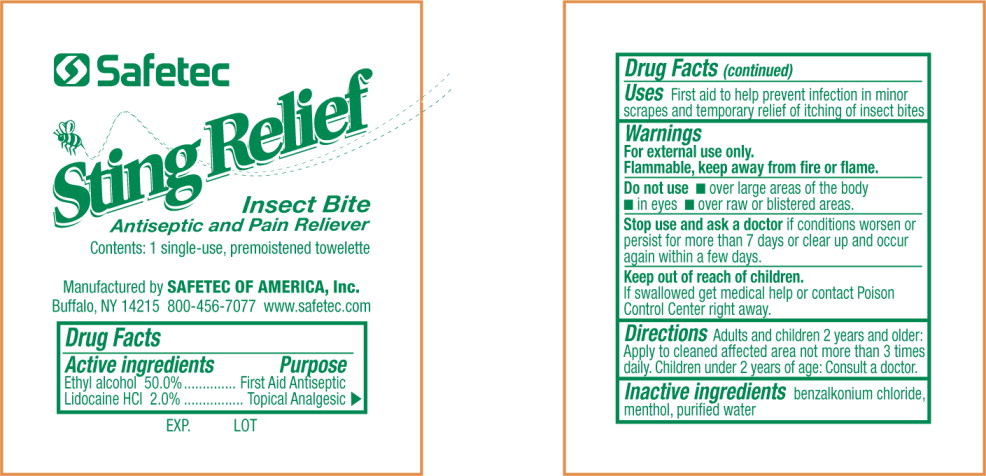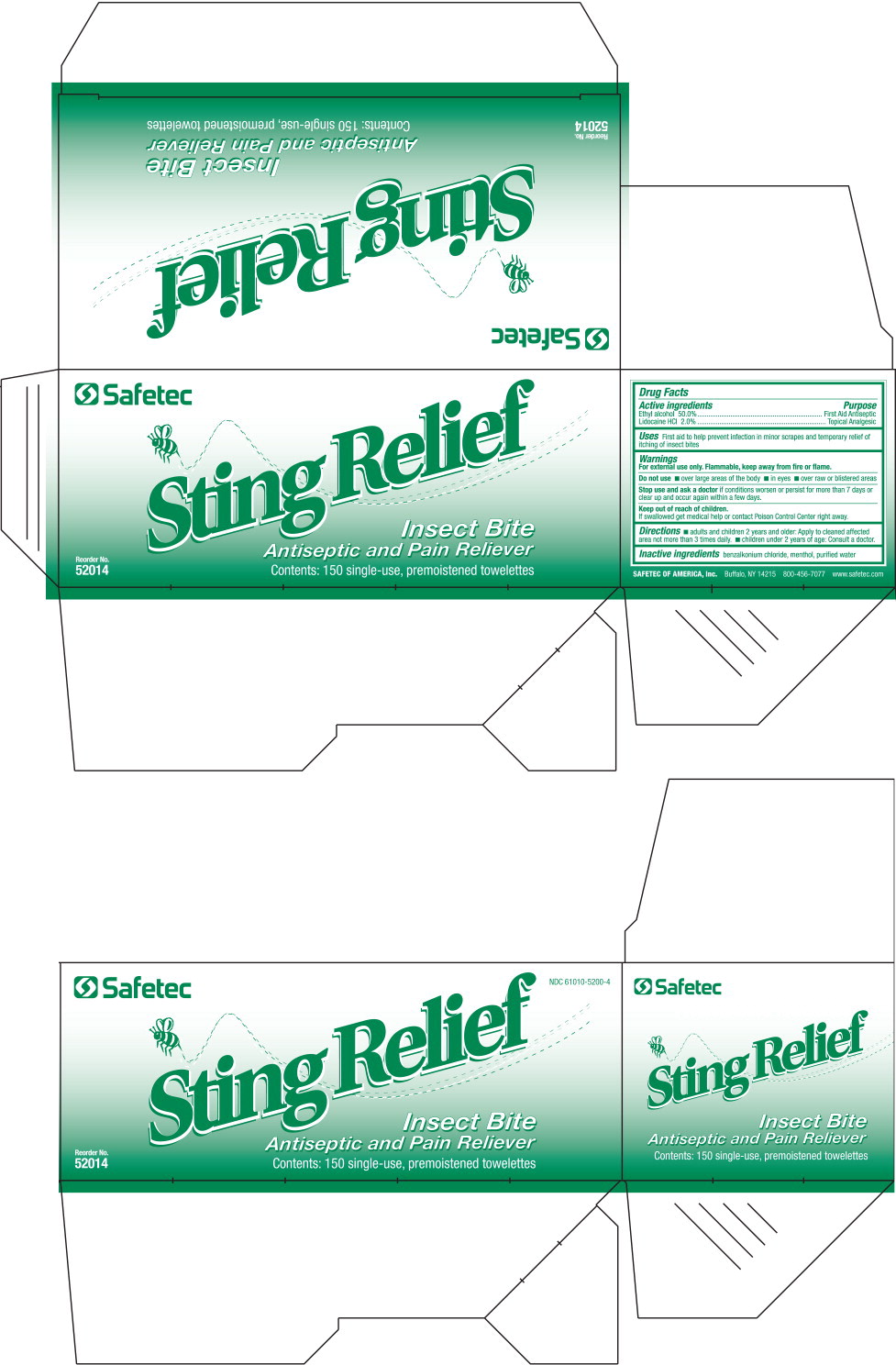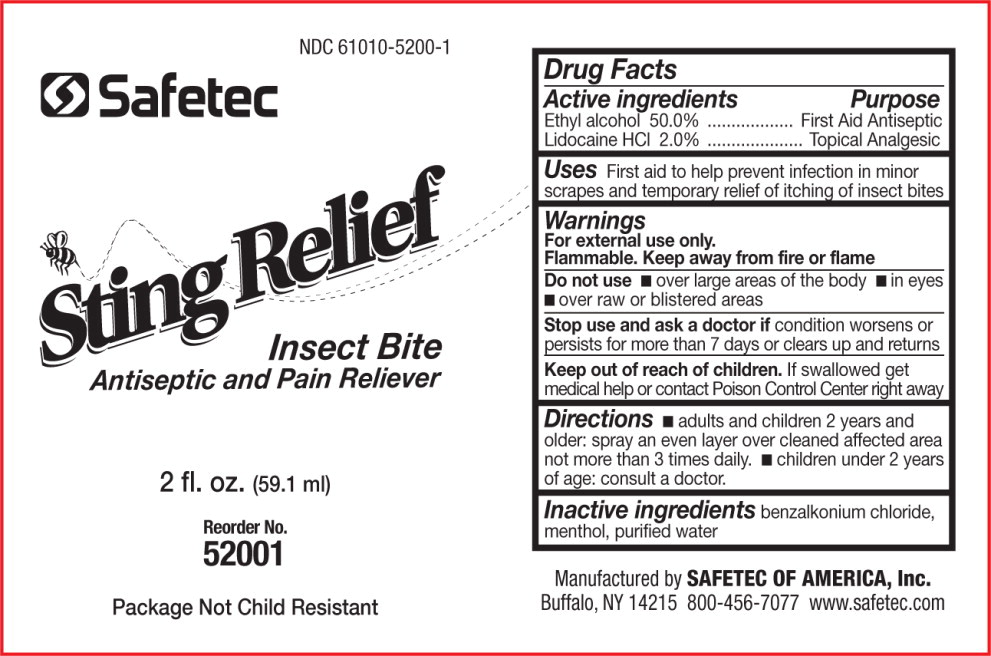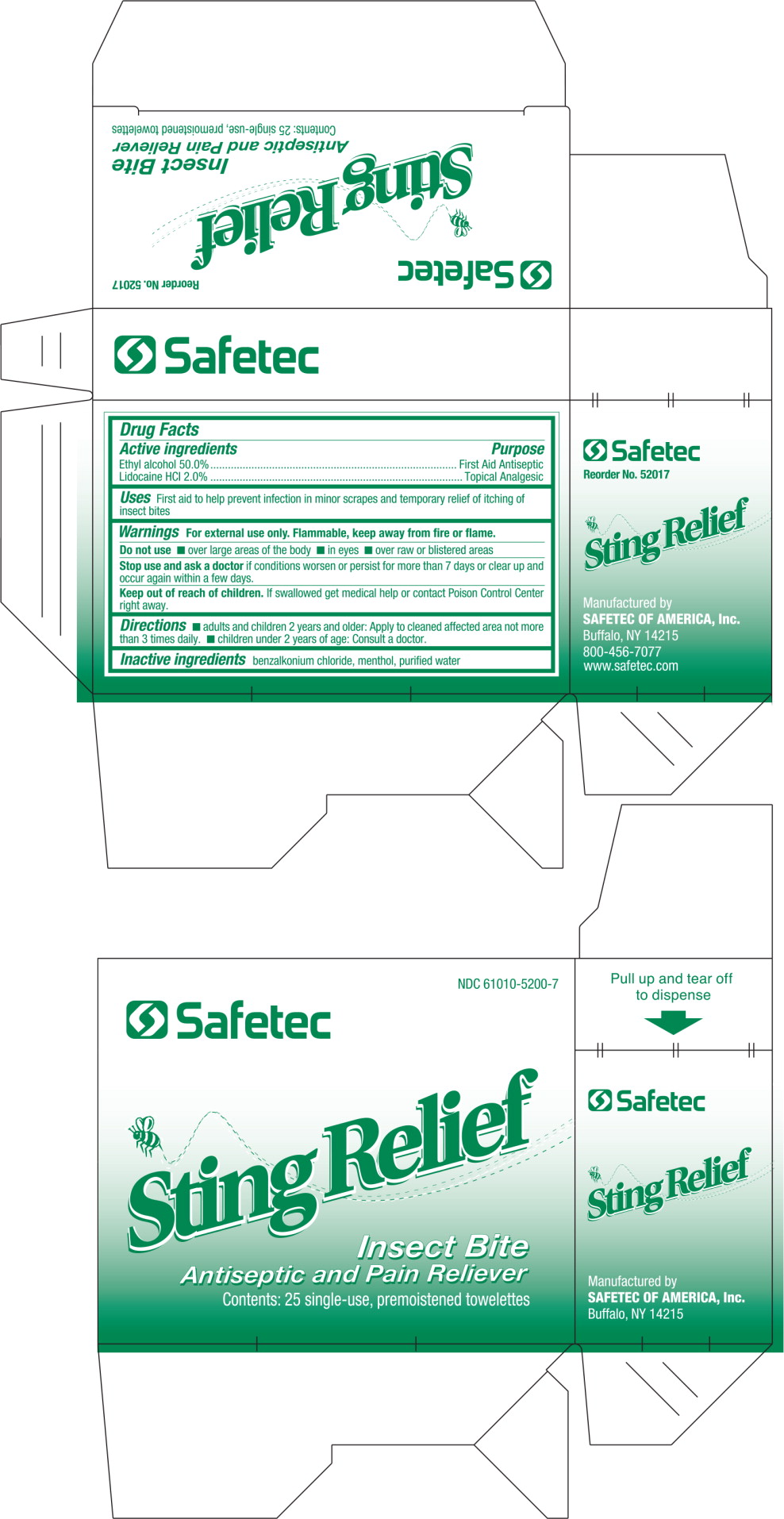 DRUG LABEL: Antiseptic
NDC: 61010-5200 | Form: LIQUID
Manufacturer: Safetec of America, Inc.
Category: otc | Type: HUMAN OTC DRUG LABEL
Date: 20240207

ACTIVE INGREDIENTS: ALCOHOL 500 mg/1 g; LIDOCAINE HYDROCHLORIDE 20 mg/1 g
INACTIVE INGREDIENTS: BENZALKONIUM CHLORIDE; MENTHOL, UNSPECIFIED FORM; WATER

61010-5200, Sting Relief

Antiseptic towelette

Drug Facts

Active Ingredients

Ethyl alcohol 50.0%

Lidocaine HCl 2.0%

Purpose

First Aid Antiseptic

Topical Analgesic

Uses

First aid to help prevent infection in minor scrapes and temporary relief of itching of insect bites

Warnings

For external use only.

Flammable, keep away from fire or flame.

Do not use

- over large areas of the body
- in eyes
- over raw or blistered areas

Stop use and ask doctorif conditions worsen or persist for more than 7 days or clear up and occur again within a few days.

Keep out of reach of children

If swallowed get medical help or contact a Poison Control Center right away

Directions

- adults and children 2 years and older: Apply to cleaned affected area not more than 3 times daily.
- children under 2 years of age: Consult a doctor.

Inactive ingredientsbenzalkonium chloride, menthol, purified water

PRINCIPAL DISPLAY PANEL – mini pouch label

Safetec

Sting Relief
Insect Bite
Antiseptic and Pain Reliever

Contents: 1 single-use, premoistened towelette

Manufactured by SAFETEC OF AMERICA, Inc.
Buffalo, NY 14215 800-456-7077 www.safetec.com

EXP. LOT

PRINCIPAL DISPLAY PANEL – 150 count box

Safetec
NDC 61010-5200-4

Sting Relief
Insect Bite
Antiseptic and Pain Reliever

Reorder No.
52004

Contents: 150 single-use, premoistened towelettes

PRINCIPAL DISPLAY PANEL – 2 fl. oz. bottle

NDC 61010-5200-1

Safetec

Sting Relief
Insect Bite
Antiseptic and Pain Reliever

2 fl. oz. (59.1 ml)

Reorder No.
52001
Package Not Child Resistant

Principal Display Panel – 25 Count Box Label

NDC 61010-5200-7

Safetec

Sting Relief

Insect Bite

Antiseptic and Pain Reliever

Contents: 25 single-use, premoistened towelettes